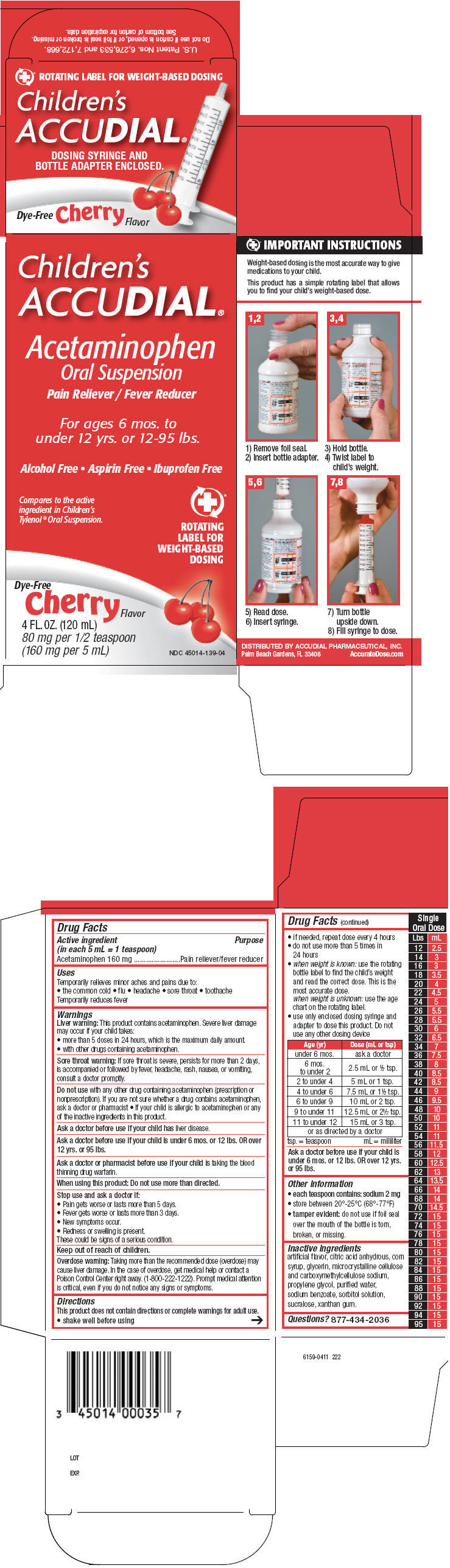 DRUG LABEL: Childrens ACCUDIAL 
NDC: 45014-139 | Form: SUSPENSION
Manufacturer: Accudial Pharmaceutical, Inc.
Category: otc | Type: HUMAN OTC DRUG LABEL
Date: 20120504

ACTIVE INGREDIENTS: Acetaminophen 160 mg/5 mL
INACTIVE INGREDIENTS: Cherry; Citric Acid Monohydrate; Corn Syrup; Glycerin; Cellulose, Microcrystalline; Carboxymethylcellulose Sodium; Propylene Glycol; Water; Sodium benzoate; Sucralose; Sorbitol; Xanthan Gum

Children's ACCUDIAL®
Pain reliever/Fever reducer

Drug Facts

Active ingredient (in each 5 mL = 1 teaspoon)

Acetaminophen 160 mg

Purpose

Pain reliever/fever reducer

Uses

Temporarily relieves minor aches and pains due to:

- the common cold
- flu
- headache
- sore throat
- toothache

Temporarily reduces fever

Warnings

Liver warning

This product contains acetaminophen. Severe liver damage may occur if your child takes:

- more than 5 doses in 24 hours, which is the maximum daily amount.
- with other drugs containing acetaminophen.

Sore throat warning

If sore throat is severe, persists for more than 2 days, is accompanied or followed by fever, headache, rash, nausea, or vomiting, consult a doctor promptly.

Do not use with any other drug containing acetaminophen (prescription or nonprescription). If you are not sure whether a drug contains acetaminophen, ask a doctor or pharmacist

- If your child is allergic to acetaminophen or any of the inactive ingredients in this product.

Ask a doctor before use if your child has liver disease.

Ask a doctor before use if your child is under 6 mos. or 12 lbs. OR over 12 yrs. or 95 lbs.

Ask a doctor or pharmacist before use if your child is taking the blood thinning drug warfarin.

When using this product: Do not use more than directed.

Stop use and ask a doctor if:

- Pain gets worse or lasts more than 5 days.
- Fever gets worse or lasts more than 3 days.
- New symptoms occur.
- Redness or swelling is present.

These could be signs of a serious condition.

Overdose warning

Taking more than the recommended dose (overdose) may cause liver damage. In the case of overdose, get medical help or contact a Poison Control Center right away. (1-800-222-1222). Prompt medical attention is critical, even if you do not notice any signs or symptoms.

Directions

This product does not contain directions or complete warnings for adult use.

- shake well before using
- if needed, repeat dose every 4 hours
- do not use more than 5 times in 24 hours
- when weight is known: use the rotating bottle label to find the child's weight and read the correct dose. This is the most accurate dose.
  when weight is unknown: use the age chart on the rotating label.
- use only enclosed dosing syringe and adapter to dose this product. Do not use any other dosing device

Age (yr) | Dose (mL or tsp)
under 6 mos. | ask a doctor
6 mos. to under 2 | 2.5 mL or ½ tsp.
2 to under 4 | 5 mL or 1 tsp.
4 to under 6 | 7.5 mL or 1½ tsp.
6 to under 9 | 10 mL or 2 tsp.
9 to under 11 | 12.5 mL or 2½ tsp.
11 to under 12 | 15 mL or 3 tsp.
or as directed by a doctor
tsp. = teaspoon
mL = milliliter

Ask a doctor before use if your child is under 6 mos. or 12 lbs. OR over 12 yrs. or 95 lbs.

Other information

- each teaspoon contains: sodium 2 mg
- store between 20°-25°C (68°-77°F)
- tamper evident: do not use if foil seal over the mouth of the bottle is torn, broken, or missing.

Inactive ingredients

artificial flavor, citric acid anhydrous, corn syrup, glycerin, microcrystalline cellulose and carboxymethylcellulose sodium, propylene glycol, purified water, sodium benzoate, sorbitol solution, sucralose, xanthan gum.

Questions?

877-434-2036

DISTRIBUTED BY ACCUDIAL PHARMACEUTICAL, INC.
Palm Beach Gardens, FL 33408

PRINCIPAL DISPLAY PANEL - 120 mL Bottle Carton

Children's
ACCUDIAL®

Acetaminophen
Oral Suspension

Pain Reliever / Fever Reducer

For ages 6 mos. to
under 12 yrs. or 12-95 lbs.

Alcohol Free • Aspirin Free • Ibuprofen Free

Compares to the active
ingredient in Children's
Tylenol® Oral Suspension.

ROTATING
LABEL FOR
WEIGHT-BASED
DOSING

Dye-Free
Cherry
Flavor

4 FL.OZ. (120 mL)
80 mg per 1/2 teaspoon
(160 mg per 5 mL)

NDC 45014-139-04